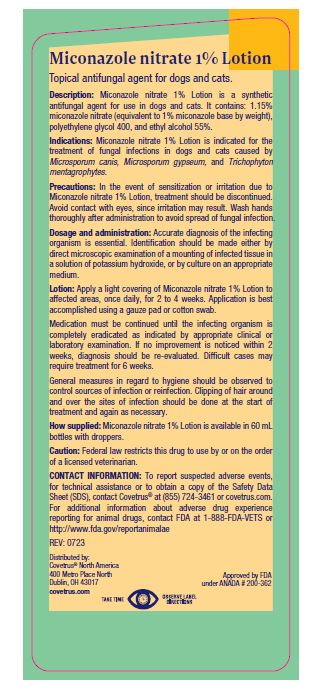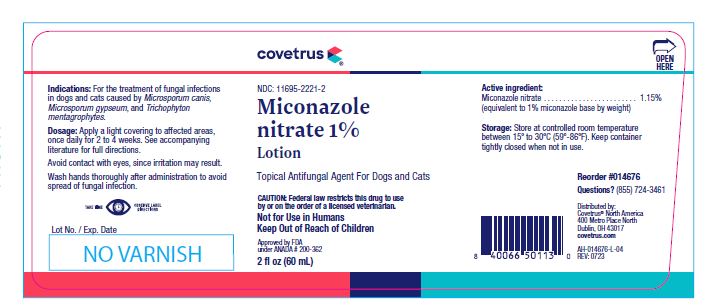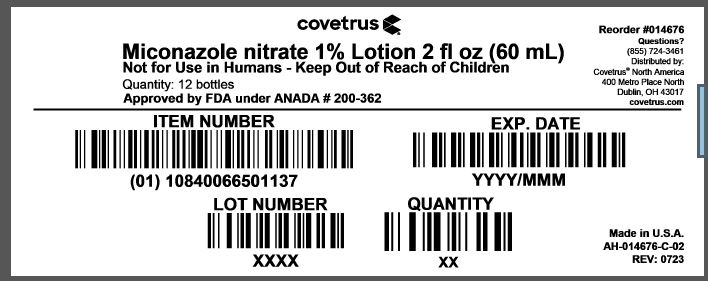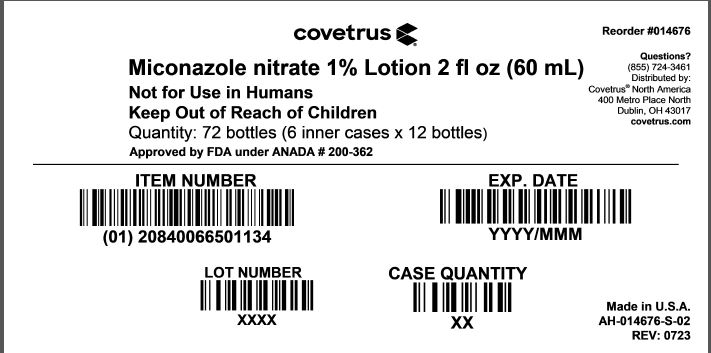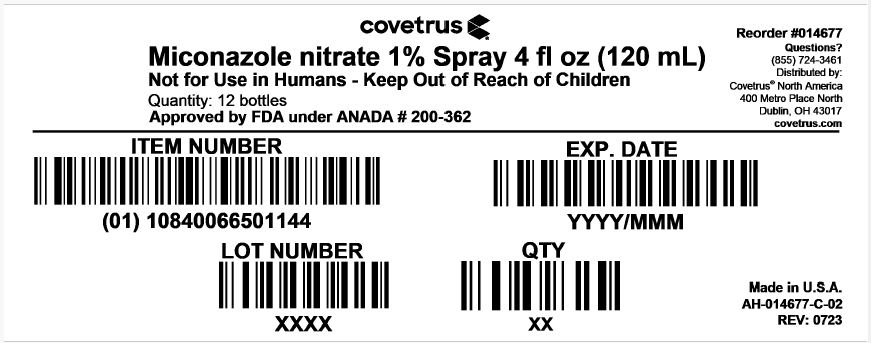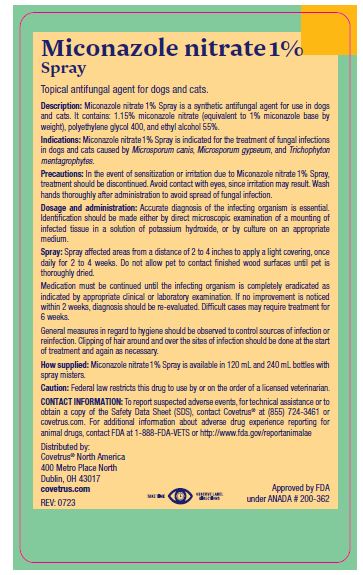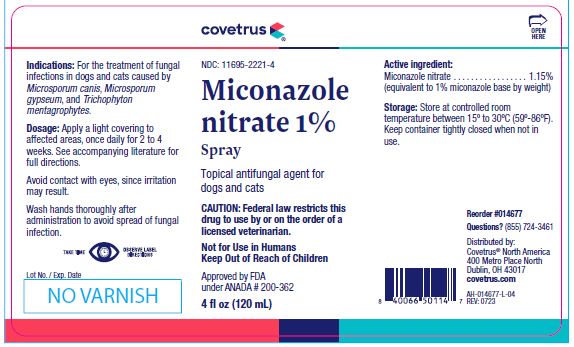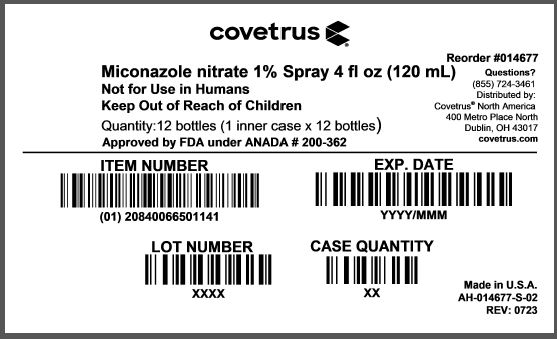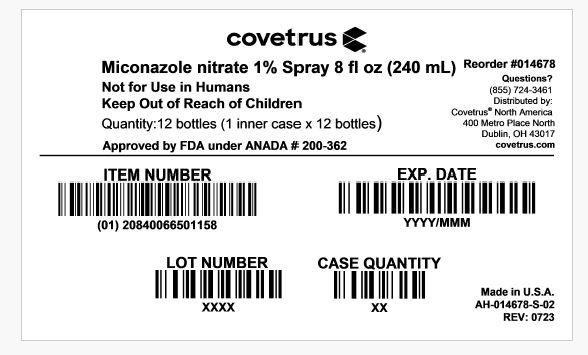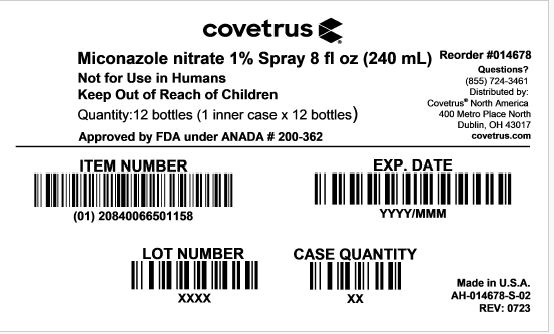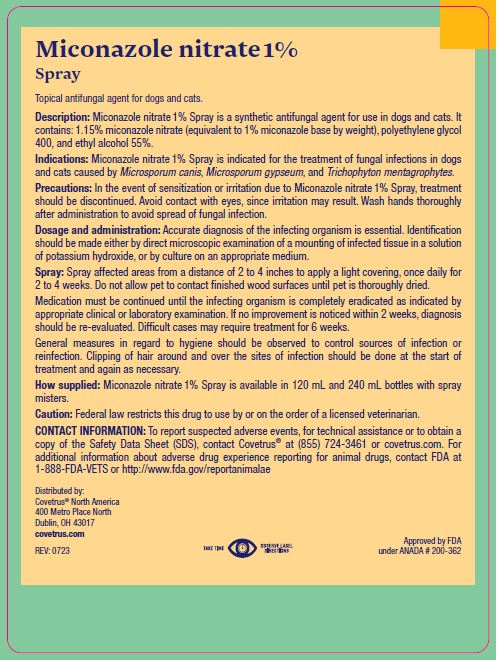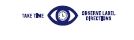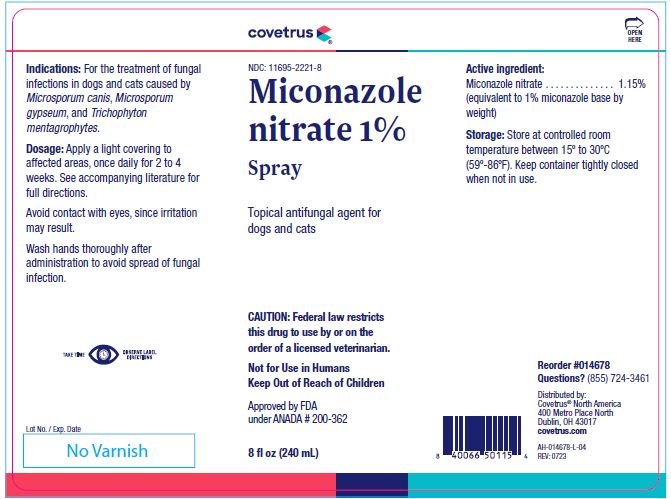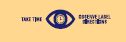 DRUG LABEL: Miconazole nitrate
NDC: 11695-2221 | Form: SPRAY
Manufacturer: Butler Animal health Supply, LLC dba Covetrus North America
Category: animal | Type: PRESCRIPTION ANIMAL DRUG LABEL
Date: 20260223

ACTIVE INGREDIENTS: MICONAZOLE NITRATE 11.5 mg/1 mL

Miconazole
nitrate 1%

VETERINARY INDICATIONS

Lotion & Spray
Topical antifungal agent for dogs and cats

PRECAUTIONS

CAUTION: Federal law restricts this drug to use by or on the order of a licensed veterinarian.

Not for Use in Humans
Keep Out of Reach of Children

Approved by FDA under ANADA # 200-362

2 fl oz (60 mL)

4 fl oz (120 mL)

8 fl oz (240 mL)

Indications:

For the treatment of fungal infections in dogs and cats caused by Microsporum canis, Microsporum gypseum, and Trichophyton mentagrophytes.

Dosage:

Apply a light covering to affected areas, once daily for 2 to 4 weeks. See accompanying literature for full directions.
Avoid contact with eyes, since irritation may result.
Wash hands thoroughly after administration to avoid spread of fungal infection.

INFORMATION FOR OWNERS/CAREGIVERS

Lot No. / Exp. Date

Active ingredient:

Miconazole nitrate . . . . . . . . . . . . . . . . . 1.15%
(equivalent to 1% miconazole base by weight)

Storage:

Store at controlled room temperature between 15º to 30ºC (59º-86ºF). Keep container tightly closed when not in use.

INFORMATION FOR OWNERS/CAREGIVERS

Reorder #014676 60 mL AH-014676-L-04 REV: 0723

Reorder #014677 120 mL AH-014677-L-04 REV: 0723

Reorder #014678 240 mL AH-014678-L-04 REV: 0723

Questions? (855) 724-3461
Distributed by:
Covetrus® North America
400 Metro Place North
Dublin, OH 43017
covetrus.com

Description:

Miconazole nitrate 1% Lotion & Spray is a synthetic antifungal agent for use in dogs and cats. It contains: 1.15% miconazole nitrate (equivalent to 1% miconazole base by weight), polyethylene glycol 400, and ethyl alcohol 55%.

Indications:

Miconazole nitrate 1% Lotion & Spray is indicated for the treatment of fungal infections in dogs and cats caused by Microsporum canis, Microsporumgypseum, and Trichophyton mentagrophytes.

Precautions:

In the event of sensitization or irritation due to Miconazole nitrate 1% Lotion & Spray, treatment should be discontinued. Avoid contact with eyes, since irritation may result. Wash hands thoroughly after administration to avoid spread of fungal infection.

Dosage and administration:

Accurate diagnosis of the infecting organism is essential. Identification should be made either by direct microscopic examination of a mounting of infected tissue in a solution of potassium hydroxide, or by culture on an appropriate medium.

Spray:

Spray affected areas from a distance of 2 to 4 inches to apply a light covering, once daily for 2 to 4 weeks. Do not allow pet to contact finished wood surfaces until pet is thoroughly dried.
Medication must be continued until the infecting organism is completely eradicated as indicated by appropriate clinical or laboratory examination. If no improvement is noticed within 2 weeks, diagnosis should be re-evaluated. Difficult cases may require treatment for 6 weeks.
General measures in regard to hygiene should be observed to control sources of infection or reinfection. Clipping of hair around and over the sites of infection should be done at the start of treatment and again as necessary.

Lotion:

Apply a light covering of Miconazole nitrate 1% Lotion to affected areas, once daily, for 2 to 4 weeks. Application is best accomplished using a gauze pad or cotton swab.
Medication must be continued until the infecting organism is completely eradicated as indicated by appropriate clinical or laboratory examination. If no improvement is noticed within 2 weeks, diagnosis should be re-evaluated. Difficult cases may require treatment for 6 weeks.
General measures in regard to hygiene should be observed to control sources of infection or reinfection. Clipping of hair around and over the sites of infection should be done at the start of treatment and again as necessary.

How supplied:

Miconazole nitrate 1% Lotion is available in 60 mL bottles with droppers.
Miconazole nitrate 1% Spray is available in 120 mL and 240 mL bottles with spray misters.

Caution:

Federal law restricts this drug to use by or on the order of a licensed veterinarian.

CONTACT INFORMATION:

To report suspected adverse events, for technical assistance or to obtain a copy of the Safety Data Sheet (SDS), contact Covetrus® at (855) 724-3461 or covetrus.com. For additional information about adverse drug experience reporting for animal drugs, contact FDA at 1-888-FDA-VETS or http://www.fda.gov/reportanimalae

INFORMATION FOR OWNERS/CAREGIVERS

Distributed by:
Covetrus® North America
400 Metro Place North
Dublin, OH 43017
covetrus.com

Approved by FDA under ANADA # 200-362